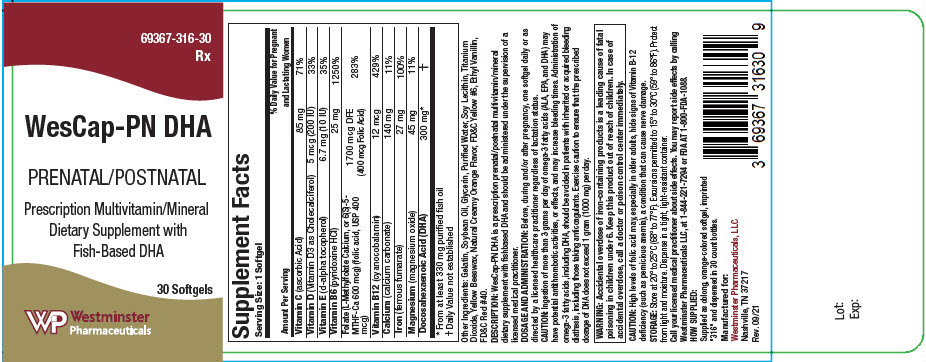 DRUG LABEL: WesCap-PN DHA
NDC: 69367-316 | Form: CAPSULE, GELATIN COATED
Manufacturer: Westminster Pharmaceuticals, LLC
Category: other | Type: DIETARY SUPPLEMENT
Date: 20211217

ACTIVE INGREDIENTS: ASCORBIC ACID 85 mg/1 1; CHOLECALCIFEROL 200 [iU]/1 1; .ALPHA.-TOCOPHEROL, D- 10 [iU]/1 1; PYRIDOXINE HYDROCHLORIDE 25 mg/1 1; LEVOMEFOLATE CALCIUM 600 ug/1 1; FOLIC ACID 400 ug/1 1; CYANOCOBALAMIN 12 ug/1 1; CALCIUM CARBONATE 140 mg/1 1; FERROUS FUMARATE 27 mg/1 1; MAGNESIUM OXIDE 45 mg/1 1; DOCONEXENT 300 mg/1 1
INACTIVE INGREDIENTS: YELLOW WAX; SOYBEAN OIL; GELATIN, UNSPECIFIED; GLYCERIN; WATER; TITANIUM DIOXIDE; LECITHIN, SOYBEAN; ETHYL VANILLATE; FD&C RED NO. 40; FD&C YELLOW NO. 6

WesCap-PN DHA

STATEMENT OF IDENTITY

Supplement Facts
Serving Size: 1 Softgel
Amount Per Serving | % Daily Value for Pregnant and Lactating Women
Vitamin C (ascorbic Acid) | 85 mg | 71%
Vitamin D (Vitamin D3 as Cholecalciferol) | 5 mcg (200 IU) | 33%
Vitamin E (d-alpha tocopherol) | 6.7 mg (10 IU) | 35%
Vitamin B6 (pyridoxine HCl) | 25 mg | 1250%
Folate (L-Methylfolate Calcium, or 6(S)-5-MTHF-Ca 600 mcg) (folic acid, USP 400 mcg) | 1700 mcg DFE (400 mcg Folic Acid) | 283%
Vitamin B12 (cyanocobalamin) | 12 mcg | 429%
Calcium (calcium carbonate) | 140 mg | 11%
Iron (ferrous fumarate) | 27 mg | 100%
Magnesium (magnesium oxide) | 45 mg | 11%
Docosahexaenoic Acid (DHA) | 300 mg [From at least 330 mg purified fish oil] | [Daily Value not established]

Other Ingredients: Gelatin, Soybean Oil, Glycerin, Purified Water, Soy Lecithin, Titanium Dioxide, Yellow Beeswax, Natural Creamy Orange Flavor, FD&C Yellow #6, Ethyl Vanillin, FD&C Red #40.

DESCRIPTION

WesCap-PN DHA is a prescription prenatal/postnatal multivitamin/mineral dietary supplement with fishbased DHA and should be administered under the supervision of a licensed medical practitioner.

DOSAGE AND ADMINISTRATION

Before, during and/or after pregnancy, one softgel daily or as directed by a licensed healthcare practitioner regardless of lactation status.

CAUTION

Ingestion of more than 3 grams per day of omega-3 fatty acids (ALA, EPA, and DHA) may have potential antithrombotic activities, or effects, and may increase bleeding times. Administration of omega-3 fatty acids, including DHA, should be avoided in patients with inherited or acquired bleeding diathesis, including those taking anticoagulants. Exercise caution to ensure that the prescribed dosage of DHA does not exceed 1 gram (1000 mg) per day.

WARNINGS

WARNING: Accidental overdose of iron-containing products is a leading cause of fatal poisoning in children under 6. Keep this product out of reach of children. In case of accidental overdose, call a doctor or poison control center immediately.

CAUTION

High levels of folic acid may, especially in older adults, hide signs of Vitamin B-12 deficiency (such as pernicious anemia), a condition that can cause nerve damage.

STORAGE

Store at 20° to 25°C (68° to 77°F). Excursions permitted to 15° to 30°C (59° to 86°F). Protect from light and moisture. Dispense in a tight, light-resistant container.

HEALTH CLAIM

Call your licensed medical practitioner about side effects. You may report side effects by calling Westminster Pharmaceuticals LLC, at 1-844-221-7294 or FDA AT 1-800-FDA-1088.

HOW SUPPLIED

Supplied as oblong, orange-colored softgel, imprinted "316" and dispensed in 30 count bottles.

HEALTH CLAIM

Manufactured for:
Westminster Pharmaceuticals, LLC
Nashville, TN 37217
Rev. 09/21

PRINCIPAL DISPLAY PANEL - 30 Softgel Bottle Label

69367-316-30
Rx

WesCap-PN DHA

PRENATAL/POSTNATAL

Prescription Multivitamin/Mineral
Dietary Supplement with
Fish-Based DHA

30 Softgels

Westminster
Pharmaceuticals